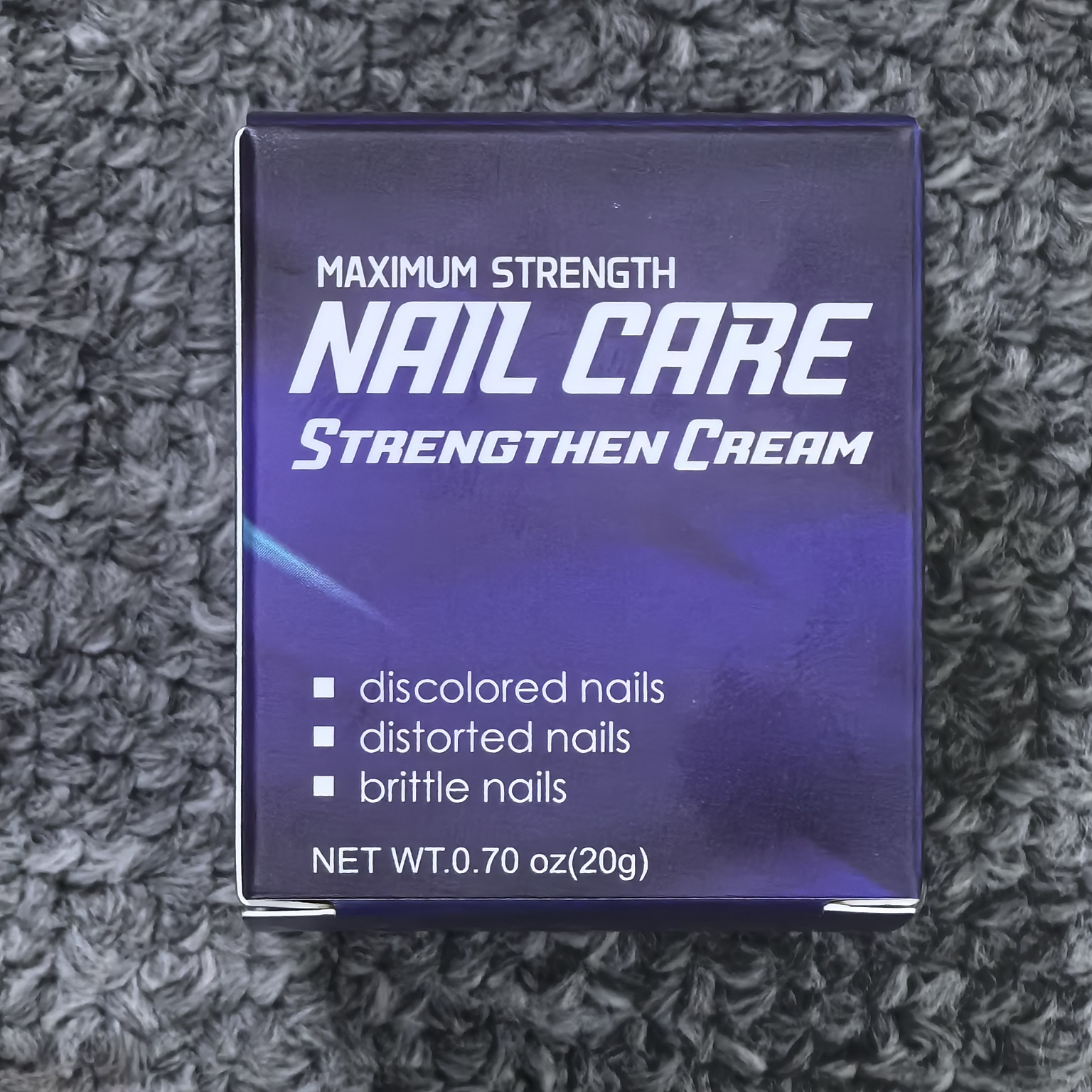 DRUG LABEL: Nail Strengthen Cream
NDC: 84117-022 | Form: CREAM
Manufacturer: Shenzhen Hengkaifeng Commerce and Trade Co., Ltd
Category: otc | Type: HUMAN OTC DRUG LABEL
Date: 20240812

ACTIVE INGREDIENTS: TOLNAFTATE 100 mg/1 g
INACTIVE INGREDIENTS: WATER

Active ingredients

Tolnaftate ≤1%

PURPOSE

Anti-fungal

Uses

Uses for relief and treatment of pain,soreness, and inflammation from nail fungus.
Symptoms: ■ discolored nails ■ brittle nails ■ distorted nails

Warnings

For external use only, some people may be sensitive to essential oils.
to determine if the product may cause any irritation. Discontinue use if any irritation occurs.
If condition worsens, discontinue use and consult a physician. Not suitable for use by children under 2 years of age without a physician's guidance.

Stop use and ask a doctor if

rash occur

Do not use

on damaged or broken skik

When using this product

Wash and thoroughly dry the affected area.
Three times a day, rub gently onto the affected area.
Wash hands after applying

Keep out of reach of children.

If swallwed, get medical help or contact a Poison Control Center right away.

inactive ingredients

Water

Propylene Glycol

Hydrogenated Castor Oil

Glycerin

Vena Sativa Peptide

Salvia Miltiorrhiza Leaf Extract

Centella Asiatica Extract

Leonurus Artemisia Powder

Arnica Montana Extract

DOSAGE & ADMINISTRATION

Wash and dry affected area thoroughly before use. Apply gently to affected area 3 times daily.